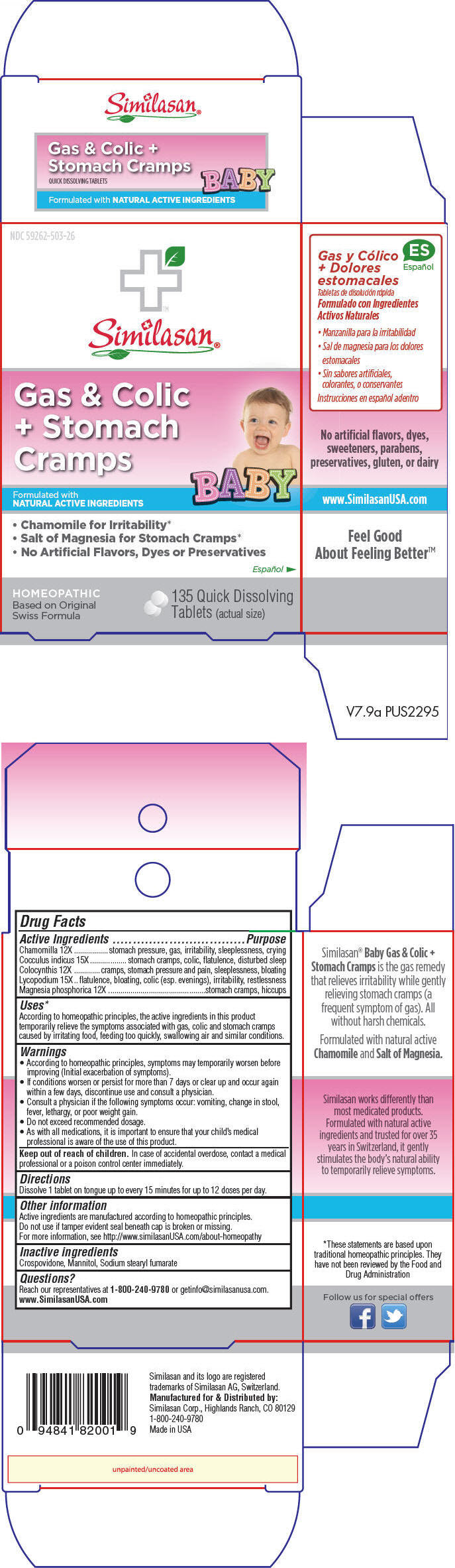 DRUG LABEL: Gas and Colic Plus Stomach Cramps Baby
NDC: 59262-503 | Form: TABLET, ORALLY DISINTEGRATING
Manufacturer: Similasan Corporation
Category: homeopathic | Type: HUMAN OTC DRUG LABEL
Date: 20180730

ACTIVE INGREDIENTS: Matricaria Chamomilla 12 [hp_X]/1 1; Anamirta Cocculus Whole 15 [hp_X]/1 1; CITRULLUS COLOCYNTHIS FRUIT PULP 12 [hp_X]/1 1; LYCOPODIUM CLAVATUM SPORE 15 [hp_X]/1 1; Magnesium Phosphate, Dibasic Trihydrate 12 [hp_X]/1 1
INACTIVE INGREDIENTS: Crospovidone, Unspecified; Sodium Stearyl Fumarate; Mannitol

Gas and Colic Plus Stomach Cramps Baby

Drug Facts

ACTIVE INGREDIENT

Active Ingredients | Purpose
Chamomilla 12X | stomach pressure, gas, irritability, sleeplessness, crying
Cocculus indicus 15X | stomach cramps, colic, flatulence, disturbed sleep
Colocynthis 12X | cramps, stomach pressure and pain, sleeplessness, bloating
Lycopodium 15X | flatulence, bloating, colic (esp. evenings), irritability, restlessness
Magnesia phosphorica 12X | stomach cramps, hiccups

Uses [These statements are based upon traditional homeopathic principles. They have not been reviewed by the Food and Drug Administration]

According to homeopathic principles, the active ingredients in this product temporarily relieve the symptoms associated with gas, colic and stomach cramps caused by irritating food, feeding too quickly, swallowing air and similar conditions.

Warnings

- According to homeopathic principles, symptoms may temporarily worsen before improving (Initial exacerbation of symptoms).
- If conditions worsen or persist for more than 7 days or clear up and occur again within a few days, discontinue use and consult a physician.
- Consult a physician if the following symptoms occur: vomiting, change in stool, fever, lethargy, or poor weight gain.
- Do not exceed recommended dosage.
- As with all medications, it is important to ensure that your child's medical professional is aware of the use of this product.

Keep out of reach of children. In case of accidental overdose, contact a medical professional or a poison control center immediately.

Directions

Dissolve 1 tablet on tongue up to every 15 minutes for up to 12 doses per day.

Other information

Active ingredients are manufactured according to homeopathic principles.

Do not use if tamper evident seal beneath cap is broken or missing.

For more information, see http://www.similasanUSA.com/about-homeopathy

Inactive ingredients

Crospovidone, Mannitol, Sodium stearyl fumarate

Questions?

Reach our representatives at 1-800-240-9780 or getinfo@similasanusa.com. www.SimilasanUSA.com

Distributed by:
Similasan Corp., Highlands Ranch, CO 80129

PRINCIPAL DISPLAY PANEL - 135 Tablet Bottle Carton

NDC 59262-503-26

Similasan®

Gas & Colic
+ Stomach
Cramps

Formulated with
NATURAL ACTIVE INGREDIENTS
BABY

- Chamomile for Irritability*
- Salt of Magnesia for Stomach Cramps*
- No Artificial Flavors, Dyes or Preservatives

HOMEOPATHIC
Based on Original
Swiss Formula

135 Quick Dissolving
Tablets (actual size)